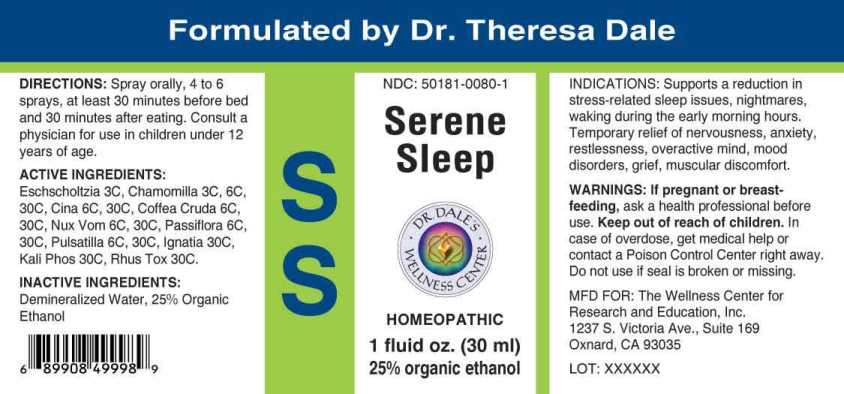 DRUG LABEL: Serene Sleep
NDC: 50181-0080 | Form: SPRAY
Manufacturer: The Wellness Center for Research a
Category: homeopathic | Type: HUMAN OTC DRUG LABEL
Date: 20250606

ACTIVE INGREDIENTS: ESCHSCHOLZIA CALIFORNICA WHOLE 3 [hp_C]/1 mL; MATRICARIA CHAMOMILLA WHOLE 3 [hp_C]/1 mL; ARTEMISIA CINA PRE-FLOWERING TOP 6 [hp_C]/1 mL; ARABICA COFFEE BEAN 6 [hp_C]/1 mL; STRYCHNOS NUX-VOMICA SEED 6 [hp_C]/1 mL; PASSIFLORA INCARNATA FLOWERING TOP 6 [hp_C]/1 mL; PULSATILLA PRATENSIS WHOLE 6 [hp_C]/1 mL; STRYCHNOS IGNATII SEED 30 [hp_C]/1 mL; DIBASIC POTASSIUM PHOSPHATE 30 [hp_C]/1 mL; TOXICODENDRON PUBESCENS LEAF 30 [hp_C]/1 mL
INACTIVE INGREDIENTS: WATER; ALCOHOL

DRUG FACTS:

ACTIVE INGREDIENTS:

Eschscholtzia Californica 3C, Chamomilla 3C, 6C, 30C, Cina 6C, 30C, Coffea Cruda 6C, 30C, Nux Vomica 6C, 30C, Passiflora Incarnata 6C, 30C, Pulsatilla (Pratensis) 6C, 30C, Ignatia Amara 30C, Kali Phosphoricum 30C, Rhus Tox 30C.

INDICATIONS:

Supports a reduction in stress-related sleep issues, nightmares, waking during the early morning hours. Temporary relief of nervousness, anxiety, restlessness. overactive mind, mood disorders, grief, muscular discomfort.

WARNINGS:

If pregnant or breast-feeding, ask a health professional before use.

Keep out of reach of children. In case of overdose, get medical help or contact a Poison Control Center right away.

Do not use if seal is broken or missing.

KEEP OUT OF REACH OF CHILDREN SECTION

Keep out of reach of children. In case of overdose, get medical help or contact a Poison Control Center right away.

DIRECTIONS:

Spray orally, 4 to 6 sprays, at least 30 minutes before bed and 30 minutes after eating. Consult a physician for use in children under 12 years of age.

INDICATIONS:

Supports a reduction in stress-related sleep issues, nightmares, waking during the early morning hours. Temporary relief of nervousness, anxiety, restlessness. overactive mind, mood disorders, grief, muscular discomfort.

INACTIVE INGREDIENTS:

Demineralized Water, 25% Organic Ethanol

QUESTIONS:

MFD FOR:

The Wellness Center for Research

and Education, Inc.

1237 S. Victoria Ave. Suite 169

Oxnard, CA 93035

PACKAGE DISPLAY LABEL:

Formulated by DR. Theresa Dale

NDC#: 50181-0080-1

Serene

Sleep

DR. DALE'S WELLNESS CENTER

Homeopathic

1 fluid oz. (30 ml)